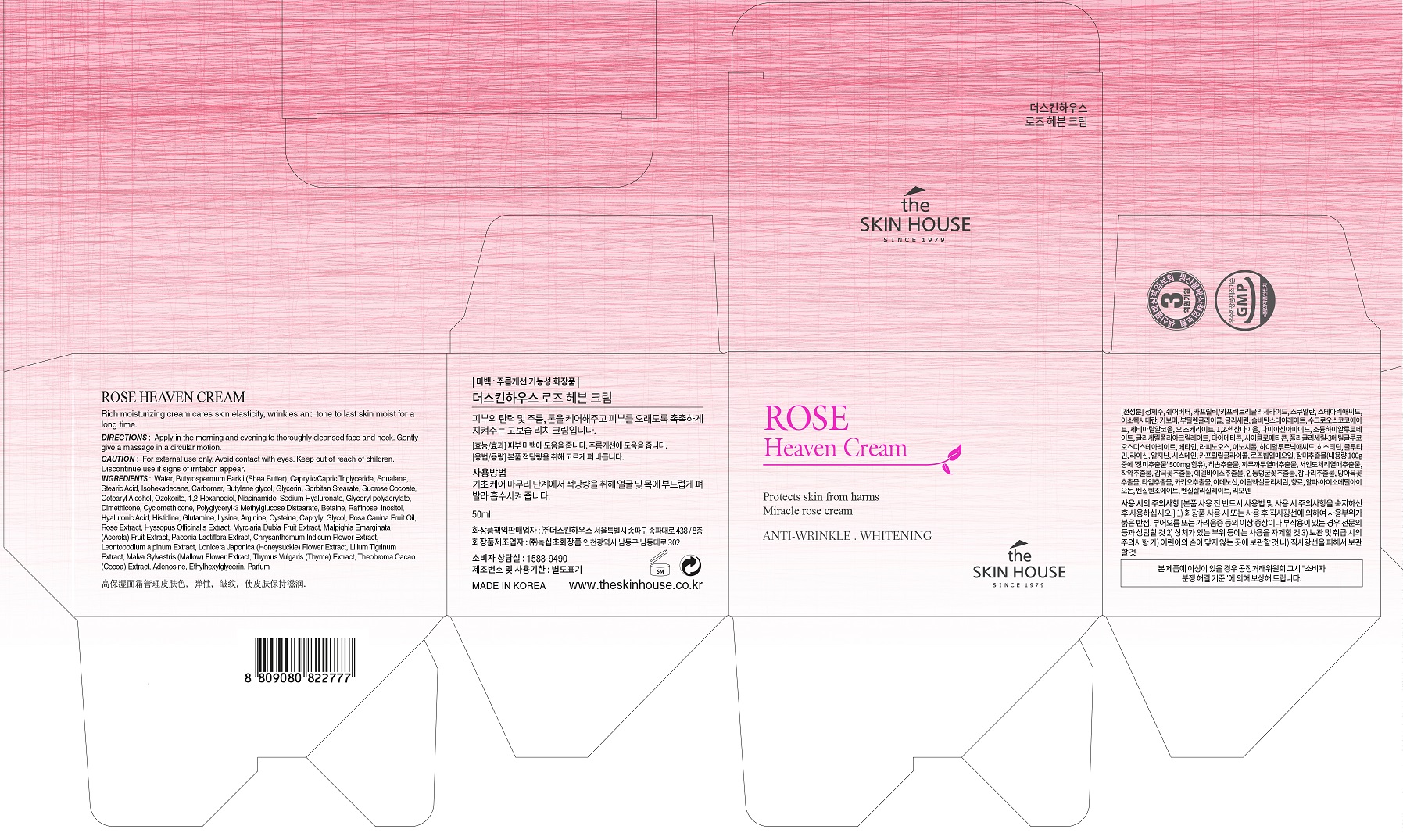 DRUG LABEL: THE SKIN HOUSE Rose HeavenCream
NDC: 73590-0022 | Form: CREAM
Manufacturer: NOKSIBCHO cosmetic Co., Ltd.
Category: otc | Type: HUMAN OTC DRUG LABEL
Date: 20200330

ACTIVE INGREDIENTS: NIACINAMIDE 2 g/100 mL; ADENOSINE 0.04 g/100 mL
INACTIVE INGREDIENTS: WATER

Drug Facts

ACTIVE INGREDIENT

Adenosine, Niacinamide

INACTIVE INGREDIENT

Butyrospermum Parkii (Shea Butter)
Caprylic/Capric Triglyceride
Squalane
Stearic Acid
Isohexadecane
Carbomer
Butylene glycol
Glycerin
Sorbitan Stearate
Sucrose Cocoate
Cetearyl Alcohol
Ozokerite
1,2-Hexanediol
Sodium Hyaluronate
Phenoxy ethanol
Glyceryl polyacrylate
Polyglyceryl-3 Methylglucose Distearate
Betaine
Raffinose
Inositol
Hyaluronic Acid
Histidine
Glutamine
Lysine
Cysteine
Caprylyl Glycol
Dimethicone
Rosa Canina Fruit Oil
Rose Extract
Hyssopus Officinalis Extract
Myrciaria Dubia Fruit Extract
Malpighia Emarginata (Acerola) Fruit Extract
Propylene Glycol
Paeonia Lactiflora Extract
Chrysanthemum Indicum Flower Extract
Leontopodium alpinum extract
Lonicera Japonica (Honeysuckle) Flower Extract
Lilium Tigrinum Extract
Malva Sylvestris (Mallow) Flower Extract
Thymus Vulgaris (Thyme) Extract
Theobroma Cacao (Cocoa) Extract
Arginine
Ethylhexylglycerin
Parfum

PURPOSE

- Anti-aging & brightening toner

A U-shape clear essence toner enables the skin to become nutritious.

Rose extracts, rose hips oil and other 14 kinds of natural extracts make the dehydrated skin to become moist, bright, smooth and more vital. Skin can absorb the toner without leaving stickiness and the toner gives a energy to skin instantly. Also, the delicate rose-scented gives elegant and classy feelings.

It is a toner which strengthens the autogenic power of skin.

keep out of reach of the children

INDICATIONS AND USAGE

apply proper amount to the skin

WARNINGS

For external use only
When using this product

■ if the following symptoms occurs after use, stop use and consult with a skin specialist

red specks, swelling, itching

■ don’t use on the part where there is injury, eczema, or dermatitis

Keep out of reach of children

■ if swallowed, get medical help or contact a person control center immediately